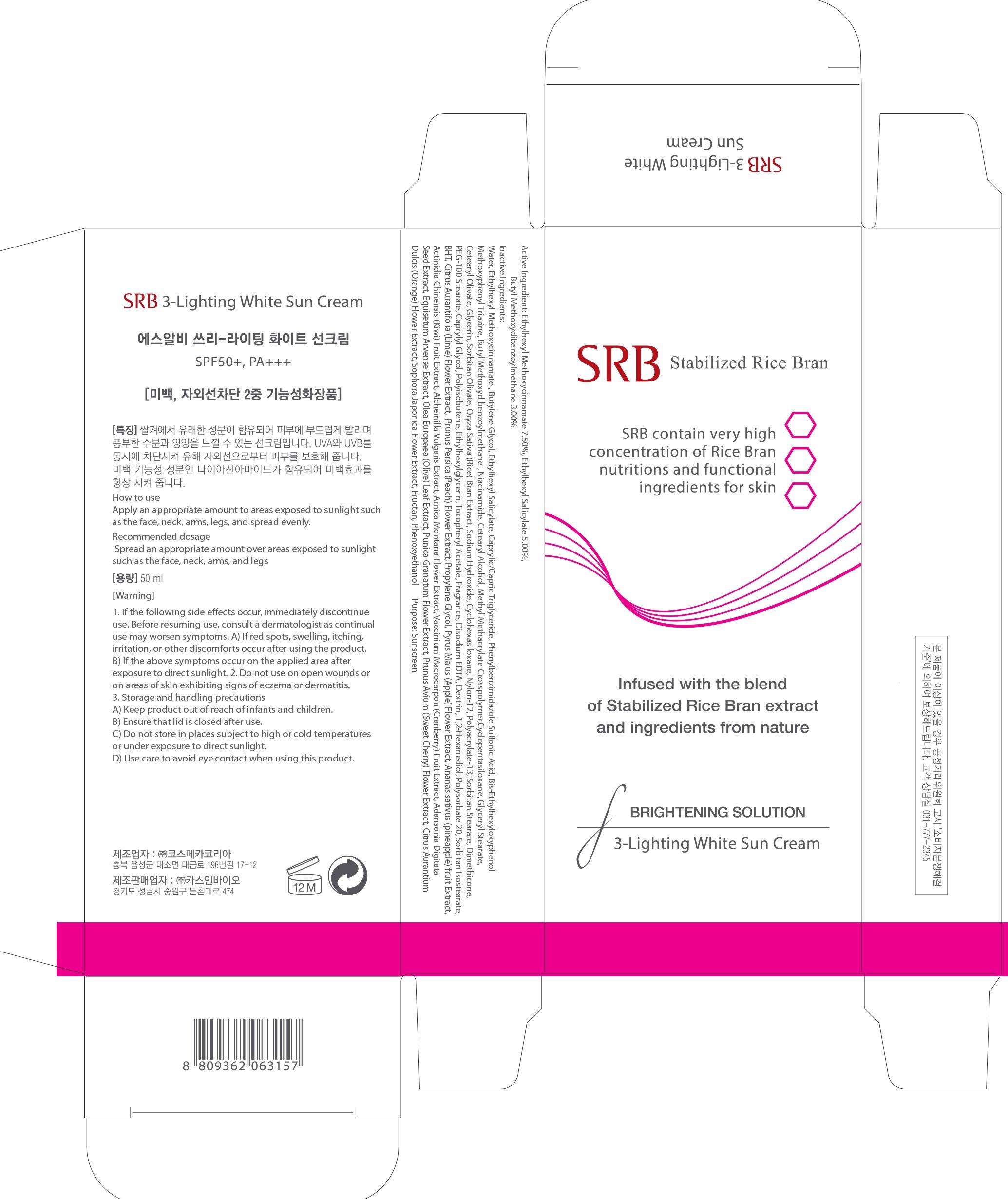 DRUG LABEL: SRB 3 Lighting White Sun
NDC: 70218-030 | Form: CREAM
Manufacturer: CASINBIO CO., LTD.
Category: otc | Type: HUMAN OTC DRUG LABEL
Date: 20151112

ACTIVE INGREDIENTS: OCTINOXATE 3.75 mg/50 mL; OCTISALATE 2.50 mg/50 mL; AVOBENZONE 1.50 mg/50 mL
INACTIVE INGREDIENTS: Water; Butylene Glycol

ACTIVE INGREDIENT

Active Ingredient: Ethylhexyl Methoxycinnamate 7.50%, Ethylhexyl Salicylate 5.00%, Butyl Methoxydibenzoylmethane 3.00%

INACTIVE INGREDIENT

Inactive Ingredients: Water, Butylene Glycol, Caprylic/Capric Triglyceride, Phenylbenzimidazole Sulfonic Acid, Bis-Ethylhexyloxyphenol Methoxyphenyl Triazine, Niacinamide, Cetearyl Alcohol, Methyl Methacrylate Crosspolymer, Cyclopentasiloxane, Glyceryl Stearate, Cetearyl Olivate, Glycerin, Sorbitan Olivate, Oryza Sativa (Rice) Bran Extract, Sodium Hydroxide, Cyclohexasiloxane, Nylon-12, Polyacrylate-13, Sorbitan Stearate, Dimethicone, PEG-100 Stearate, Caprylyl Glycol, Polyisobutene, Ethylhexylglycerin, Tocopheryl Acetate, Fragrance, Disodium EDTA, Dextrin, 1,2-Hexanediol, Polysorbate 20, Sorbitan Isostearate, BHT, Citrus Aurantifolia (Lime) Flower Extract, Prunus Persica (Peach) Flower Extract, Propylene Glycol, Pyrus Malus (Apple) Flower Extract, Ananas sativus (pineapple) fruit Extract, Actinidia Chinensis (Kiwi) Fruit Extract, Alchemilla Vulgaris Extract, Arnica Montana Flower Extract, Vaccinium Macrocarpon (Cranberry) Fruit Extract, Adansonia Digitata Seed Extract, Equisetum Arvense Extract, Olea Europaea (Olive) Leaf Extract, Punica Granatum Flower Extract, Prunus Avium (Sweet Cherry) Flower Extract, Citrus Aurantium Dulcis (Orange) Flower Extract, Sophora Japonica Flower Extract, Fructan, Phenoxyethanol

PURPOSE

Purpose: Sunscreen

WARNINGS

Warnings: 1. If the following side effects occur, immediately discontinue use. Before resuming use, consult a dermatologist as continual use may worsen symptoms. A) If red spots, swelling, itching, irritation, or other discomforts occur after using the product. B) If the above symptoms occur on the applied area after exposure to direct sunlight. 2. Do not use on open wounds or on areas of skin exhibiting signs of eczema or dermatitis. 3. Storage and handling precautions A) Keep product out of reach of infants and children. B) Ensure that lid is closed after use. C) Do not store in places subject to high or cold temperatures or under exposure to direct sunlight. D) Use care to avoid eye contact when using this product.

DESCRIPTION

How to use: Apply an appropriate amount to areas exposed to sunlight such as the face, neck, arms, legs, and spread evenly.

Recommended dosage: Spread an appropriate amount over areas exposed to sunlight such as the face, neck, arms, and legs